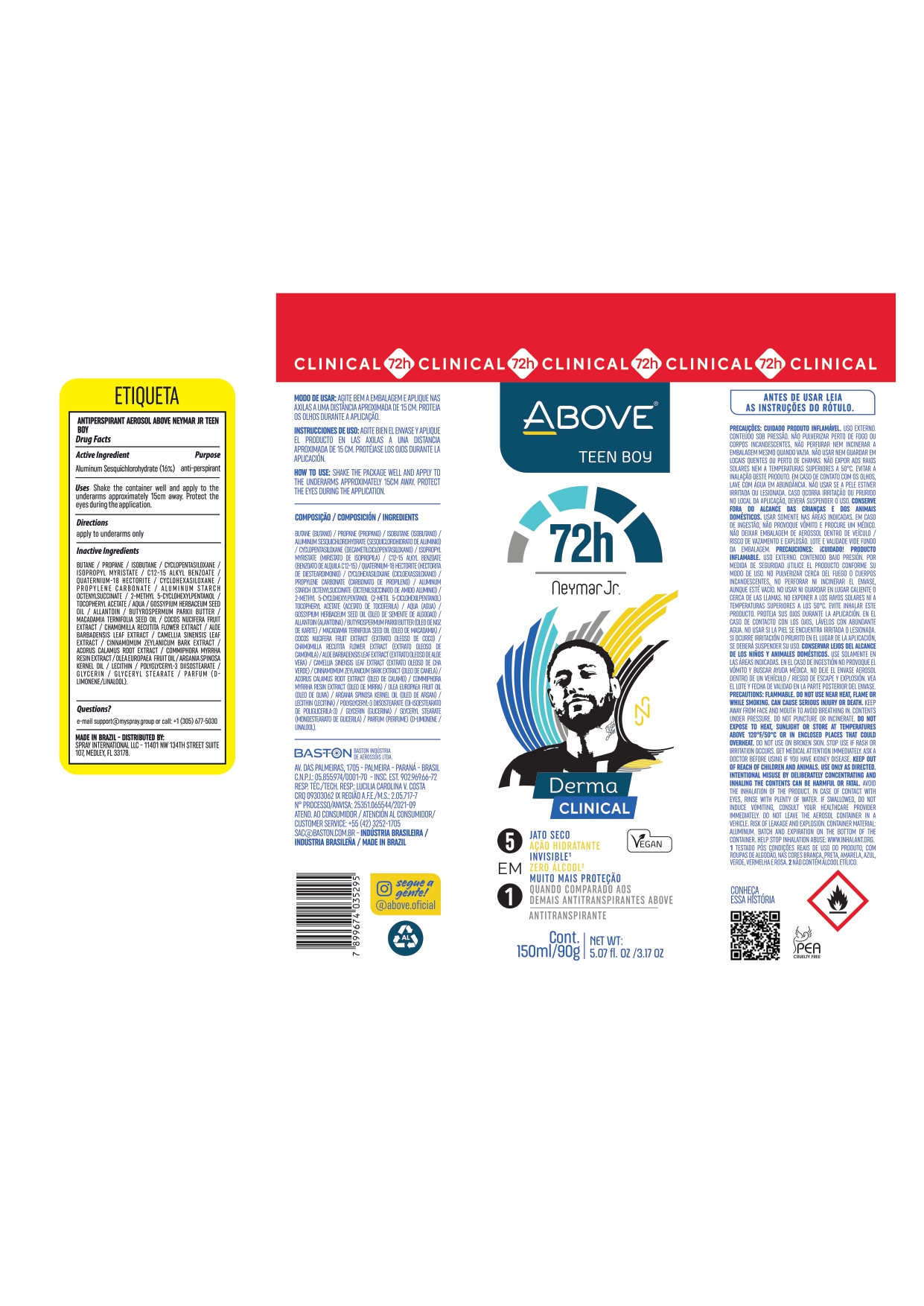 DRUG LABEL: ANTIPERSPIRANT ABOVE NEYMAR JR TEEN BOY
NDC: 73306-1128 | Form: AEROSOL
Manufacturer: BASTON INDUSTRIA DE AEROSSOIS LTDA
Category: otc | Type: HUMAN OTC DRUG LABEL
Date: 20241009

ACTIVE INGREDIENTS: ALUMINUM SESQUICHLOROHYDRATE 24 g/100 g
INACTIVE INGREDIENTS: CYCLOMETHICONE 6; MYRRH; ARGAN OIL; GLYCERIN; GLYCERYL MONOSTEARATE; PROPANE; 2-METHYL 5-CYCLOHEXYLPENTANOL; CYCLOMETHICONE 5; ISOPROPYL MYRISTATE; ALKYL (C12-15) BENZOATE; ALUMINUM STARCH OCTENYLSUCCINATE; ALLANTOIN; ACORUS CALAMUS ROOT; CINNAMON BARK OIL; BUTANE; ALOE VERA LEAF; GREEN TEA LEAF; POLYGLYCERYL-3 DIISOSTEARATE; QUATERNIUM-18 HECTORITE; ISOBUTANE; MACADAMIA OIL; .ALPHA.-TOCOPHEROL ACETATE; WATER

ANTIPERSPIRANT ABOVE NEYMAR JR TEEN BOY

ALUMINUM SESQUICHLOROHYDRATE 24 %

ANTIPERSPIRANT DEODORANT

DOSAGE AND ADMINISTRATION

SHAKE WELL AND APPLY TO THE ARMPITS FROM A DISTANCE OF ABOUT 15 CM. PROTECT YOUR EYES DURING APPLICATION

BUTANE PROPANE ISOBUTANE ALUMINUM SESQUICHLOROHYDRATE CYCLOPENTASILOXANE ISOPROPYL MYRISTATE C12-15 ALKYL BENZOATE PARFUM QUATERNIUM-18 HECTORITE CYCLOHEXASILOXANE PROPYLENE CARBONATE ALUMINUM STARCH OCTENYLSUCCINATE 2-METHYL 5-CYCLOHEXYLPENTANOL TOCOPHERYL ACETATE AQUA GOSSYPIUM HERBACEUM SEED OIL ALLANTOIN BUTYROSPERMUM PARKII BUTTER MACADAMIA TERNIFOLIA SEED OIL COCOS NUCIFERA FRUIT EXTRACT CHAMOMILLA RECUTITA FLOWER EXTRACT ALOE BARBADENSIS LEAF EXTRACT CAMELLIA SINENSIS LEAF EXTRACT CINNAMOMUM ZEYLANICUM BARK EXTRACT ACORUS CALAMUS ROOT EXTRACT COMMIPHORA MYRRHA RESIN EXTRACT OLEA EUROPAEA FRUIT OIL ARGANIA SPINOSA KERNEL OIL LECITHIN POLYGLYCERYL-3 DIISOSTEARATE GLYCERIN GLYCERYL STEARATE

BUTANE
PROPANE
ISOBUTANE
ALUMINUM SESQUICHLOROHYDRATE
CYCLOPENTASILOXANE
ISOPROPYL MYRISTATE
C12-15 ALKYL BENZOATE
PARFUM
QUATERNIUM-18 HECTORITE
CYCLOHEXASILOXANE
PROPYLENE CARBONATE
ALUMINUM STARCH OCTENYLSUCCINATE
2-METHYL 5-CYCLOHEXYLPENTANOL
TOCOPHERYL ACETATE
AQUA
GOSSYPIUM HERBACEUM SEED OIL
ALLANTOIN
BUTYROSPERMUM PARKII BUTTER
MACADAMIA TERNIFOLIA SEED OIL
COCOS NUCIFERA FRUIT EXTRACT
CHAMOMILLA RECUTITA FLOWER EXTRACT
ALOE BARBADENSIS LEAF EXTRACT
CAMELLIA SINENSIS LEAF EXTRACT
CINNAMOMUM ZEYLANICUM BARK EXTRACT
ACORUS CALAMUS ROOT EXTRACT
COMMIPHORA MYRRHA RESIN EXTRACT
OLEA EUROPAEA FRUIT OIL
ARGANIA SPINOSA KERNEL OIL
LECITHIN
POLYGLYCERYL-3 DIISOSTEARATE
GLYCERIN
GLYCERYL STEARATE

EMAIL : SAC@BASTON.COM.BR

KEEP OUT OF CHILDREN

RECENT MAJOR CHANGES

SHAKE WELL AND APPLY TO THE ARMPITS FROM A DISTANCE OF ABOUT 15 CM. PROTECT YOUR EYES DURING APPLICATION

FLAMABLE DO NOT USE NEAR HEAT , FLAME OR WHILE SMOKING. CAN CAUSE SERIOUS INJURY OR DEATH . KEEP AWAY FROM FACE AND MOUTH TO AVOID BREATHING IN . AVOID SPARAYING IN THE EYES

FLAMABLE DO NOT USE NEAR HEAT , FLAME OR WHILE SMOKING. CAN CAUSE SERIOUS INJURY OR DEATH .
KEEP AWAY FROM FACE AND MOUTH TO AVOID BREATHING IN . AVOID SPRAYING IN THE EYES